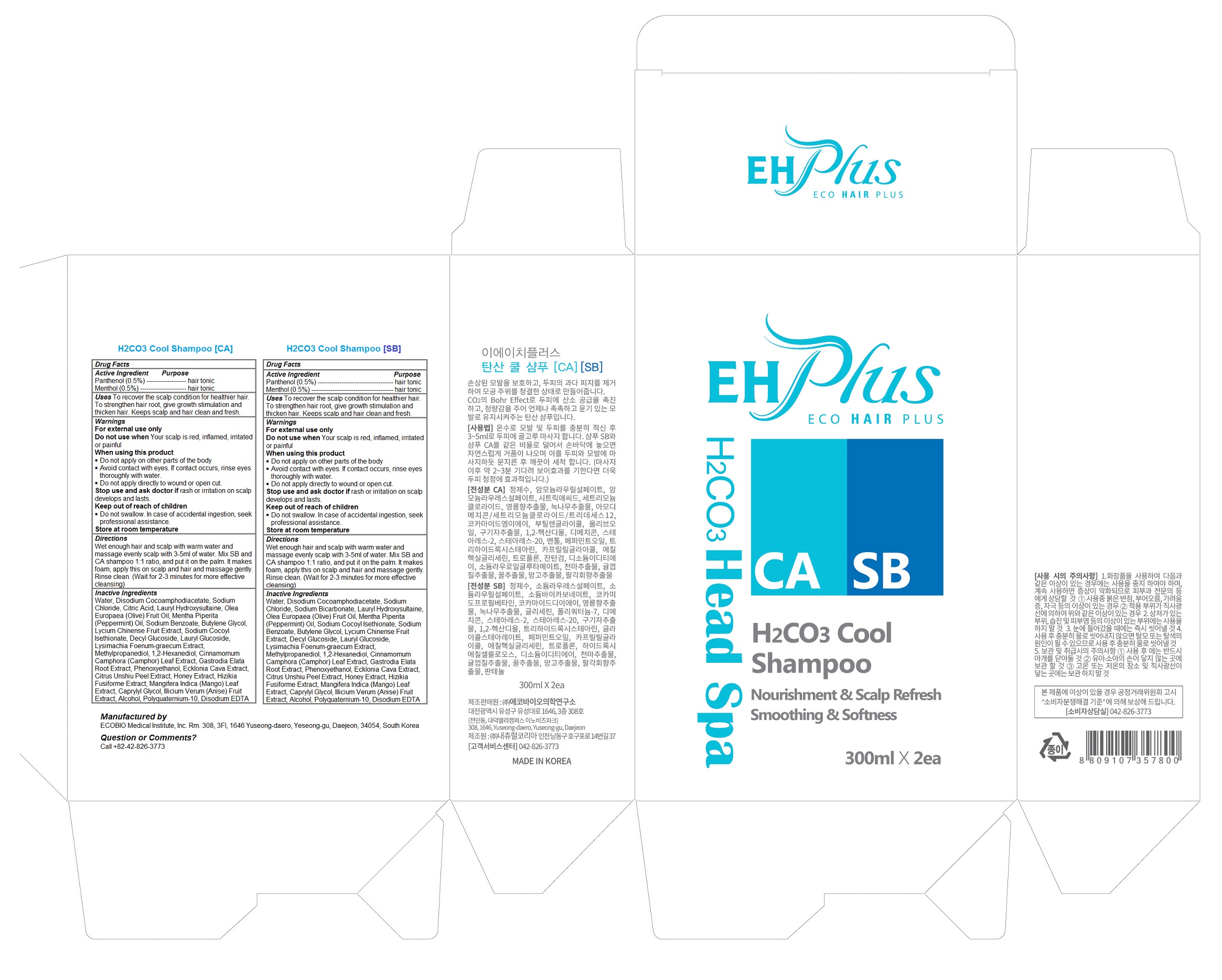 DRUG LABEL: EH Plus H2CO3 Cool
NDC: 70937-104 | Form: KIT | Route: TOPICAL
Manufacturer: ECOBIO Medical Institute, Inc.
Category: otc | Type: HUMAN OTC DRUG LABEL
Date: 20161017

ACTIVE INGREDIENTS: PANTHENOL 1.5 g/300 mL; MENTHOL 1.5 g/300 mL; PANTHENOL 1.5 g/300 mL; MENTHOL 1.5 g/300 mL
INACTIVE INGREDIENTS: WATER; DISODIUM COCOAMPHODIACETATE; Sodium Chloride; SODIUM BICARBONATE; LAURYL HYDROXYSULTAINE; OLIVE OIL; PEPPERMINT OIL; SODIUM COCOYL ISETHIONATE; BUTYLENE GLYCOL; LYCIUM CHINENSE FRUIT; DECYL GLUCOSIDE; LAURYL GLUCOSIDE; METHYLPROPANEDIOL; 1,2-HEXANEDIOL; CINNAMOMUM CAMPHORA LEAF; GASTRODIA ELATA TUBER; PHENOXYETHANOL; ECKLONIA CAVA; TANGERINE PEEL; HONEY; SARGASSUM FUSIFORME; MANGIFERA INDICA LEAF; Caprylyl Glycol; STAR ANISE FRUIT; Alcohol; POLYQUATERNIUM-10 (1000 MPA.S AT 2%); EDETATE DISODIUM ANHYDROUS; WATER; DISODIUM COCOAMPHODIACETATE; Sodium Chloride; CITRIC ACID MONOHYDRATE; LAURYL HYDROXYSULTAINE; OLIVE OIL; PEPPERMINT OIL; SODIUM BENZOATE; Butylene Glycol; LYCIUM CHINENSE FRUIT; SODIUM COCOYL ISETHIONATE; DECYL GLUCOSIDE; LAURYL GLUCOSIDE; Methylpropanediol; 1,2-Hexanediol; CINNAMOMUM CAMPHORA LEAF; GASTRODIA ELATA TUBER; Phenoxyethanol; ECKLONIA CAVA; TANGERINE PEEL; HONEY; SARGASSUM FUSIFORME; MANGIFERA INDICA LEAF; Caprylyl Glycol; STAR ANISE FRUIT; Alcohol; POLYQUATERNIUM-10 (1000 MPA.S AT 2%); EDETATE DISODIUM ANHYDROUS

EH Plus H2CO3 Cool Shampoo

Active Ingredients

H2CO3 Cool Shampoo SB

Panthenol (0.5%)

Menthol (0.5%)

H2CO3 Cool Shampoo CA

Panthenol (0.5%)

Menthol (0.5%)

Purpose

Hair Tonic

Keep out of reach of children

Do not swallow. In case of accidental ingestion, seek professional assistance.

Uses

To recover the scalp condition for healthier hair. To strengthen hair root, give growth stimulation and thicken hair. Keeps scalp and hair clean and fresh.

Warnings

For external use only
Do not use when Your scalp is red, inflamed, irritated or painful
When using this product
- Do not apply on other parts of the body
- Avoid contact with eyes. If contact occurs, rinse eyes thoroughly with water.
- Do not apply directly to wound or open cut.
Stop use and ask doctor if rash or irritation on scalp develops and lasts.
Store at room temperature

Directions

Wet enough hair and scalp with warm water and massage evenly scalp with 3-5ml of water. Mix SB and CA shampoo 1:1 ratio, and put it on the palm. It makes foam, apply this on scalp and hair and massage gently. Rinse clean. (Wait for 2-3 minutes for more effective cleansing)

Inactive Ingredients

H2CO3 Cool Shampoo SB

Water, Disodium Cocoamphodiacetate, Sodium Chloride, Sodium Bicarbonate, Lauryl Hydroxysultaine, Olea Europaea (Olive) Fruit Oil, Mentha Piperita (Peppermint) Oil, Sodium Cocoyl Isethionate, Sodium Benzoate, Butylene Glycol, Lycium Chinense Fruit Extract, Decyl Glucoside, Lauryl Glucoside, Lysimachia Foenum-graecum Extract, Methylpropanediol, 1,2-Hexanediol, Cinnamomum Camphora (Camphor) Leaf Extract, Gastrodia Elata Root Extract, Phenoxyethanol, Ecklonia Cava Extract, Citrus Unshiu Peel Extract, Honey Extract, Hizikia Fusiforme Extract, Mangifera Indica (Mango) Leaf Extract, Caprylyl Glycol, Illicium Verum (Anise) Fruit Extract, Alcohol, Polyquaternium-10, Disodium EDTA

H2CO3 Cool Shampoo CA

Water, Disodium Cocoamphodiacetate, Sodium Chloride, Citric Acid, Lauryl Hydroxysultaine, Olea Europaea (Olive) Fruit Oil, Mentha Piperita (Peppermint) Oil, Sodium Benzoate, Butylene Glycol, Lycium Chinense Fruit Extract, Sodium Cocoyl Isethionate, Decyl Glucoside, Lauryl Glucoside, Lysimachia Foenum-graecum Extract, Methylpropanediol, 1,2-Hexanediol, Cinnamomum Camphora (Camphor) Leaf Extract, Gastrodia Elata Root Extract, Phenoxyethanol, Ecklonia Cava Extract, Citrus Unshiu Peel Extract, Honey Extract, Hizikia Fusiforme Extract, Mangifera Indica (Mango) Leaf Extract, Caprylyl Glycol, Illicium Verum (Anise) Fruit Extract, Alcohol, Polyquaternium-10, Disodium EDTA